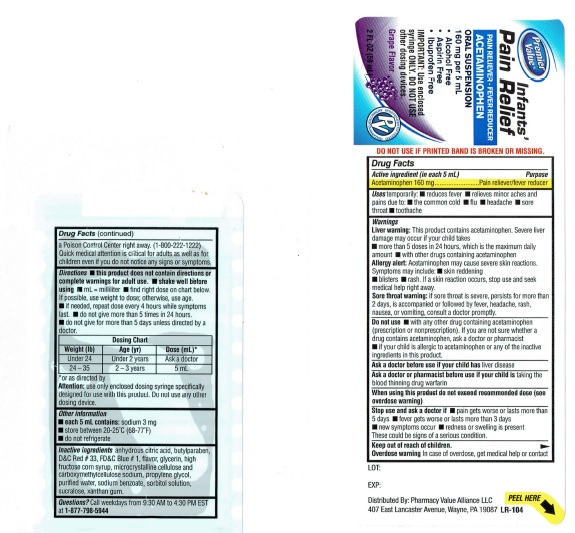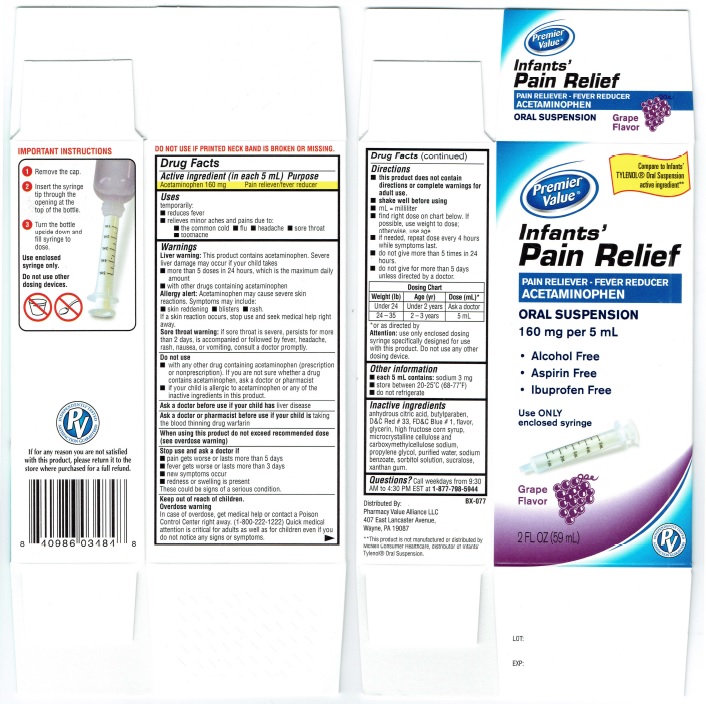 DRUG LABEL: Infants Pain Relief Oral Suspension Grape Flavor
NDC: 68016-242 | Form: SUSPENSION
Manufacturer: Pharmacy Value Alliance, LLC
Category: otc | Type: HUMAN OTC DRUG LABEL
Date: 20181024

ACTIVE INGREDIENTS: ACETAMINOPHEN 160 mg/5 mL
INACTIVE INGREDIENTS: ANHYDROUS CITRIC ACID; BUTYLPARABEN; D&C RED NO. 33; FD&C BLUE NO. 1; GLYCERIN; HIGH FRUCTOSE CORN SYRUP; MICROCRYSTALLINE CELLULOSE; CARBOXYMETHYLCELLULOSE SODIUM; PROPYLENE GLYCOL; WATER; SODIUM BENZOATE; SORBITOL; SUCRALOSE; XANTHAN GUM

Infants' Pain Relief Oral Suspension Grape Flavor

Drug Facts

Active ingredient (in each 5 mL) Acetaminophen 160 mg

Purpose Pain reliever/fever reducer

INDICATIONS AND USAGE

Uses temporarily:

■ reduces fever
■ relieves minor aches and pains due to:
■ the common cold ■ flu ■ headache ■ sore throat
■ toothache

Warnings
Liver warning: This product contains acetaminophen. Severe
liver damage may occur if your child takes
■ more than 5 doses in 24 hours, which is the maximum daily
amount
■ with other drugs containing acetaminophen

Allergy alert: Acetaminophen may cause severe skin
reactions. Symptoms may include:
■ skin reddening. blisters. rash.
If askin reaction occurs, stop use and seek medical help right
away.

Sore throat warning: if sore throat is severe, persists for more
than 2 days, is accompanied or followed by fever, headache,
rash, nausea, or vomiting, consult a doctor promptly.

Do not use
■ with any other drug containing acetaminophen (prescription
or nonprescription). If you are not sure whether adrug
contains acetaminophen, ask a doctor or pharmacist
■ if your child is allergic to acetaminophen or any of the
inactive ingredients in this product.

Ask a doctor before use if your child has liver disease

Ask a doctor or pharmacist before use if your child is taking
the blood thinning drug warfarin

When using this product do not exceed recommended dose
(see overdose warning)

Stop use and ask a doctor if
■ pain gets worse or lasts more than 5 days
■ fever gets worse or lasts more than 3 days
■ new symptoms occur
■ redness or swelling is present
These could be signs of a serious condition.

Keep out of reach of children

OVERDOSAGE

Overdose warning
In case of overdose, get medical help or contact a Poison
Control Center right away. (1-800-222-1222) Quick medical
attention is critical for adults as well as for children even if you
do not notice any signs or symptoms.

Directions
■ this product does not contain
directions or complete warnings for
adult use.
■ shake well before using
■ mL = milliliter
■ find right dose on chart below. If
possible, use weight to dose;
otherwise, use age.
■ if needed, repeat dose every 4 hours
while symptoms last.
■ do not give more than 5 times in 24
hours.
■ do not give for more than 5 days

Dosing Chart
Weight (lb) | Age (yr) | Dose (mL)*
Under 24 | Under 2 years | Ask a doctor
24 - 35 | 2 -3 years | 5 mL

*or as directed by
Attention: use only enclosed dosing
syringe specifically designed for use
with this product. Do not use any other
dosing device.

Other information
■ each 5 ml contains: sodium 3 mg
■ store between 20-25°C (68-7TF)
■ do not refrigerate

Inactive ingredients
anhydrous citric acid, butylparaben,
D&C Red # 33, FD&C Blue # 1, flavor,
glycerin, high fructose corn syrup,
microcrystalline cellulose and
carboxymethylcellulose sodium,
propylene glycol, purified water, sodium
benzoate, sorbitol solution, sucralose,
xanthan gum.

Questions? Call weekdays from 9:30
AM to 4:30 PM EST at 1-877-798-5944

Principal Display Panel

Premier

Value®

Infants'

Pain Relief

PAIN RELIEVER - FEVER REDUCER

ACETAMINOPHEN

ORAL SUSPENSION

Grape Flavor

Premier

Value®

Compare to Infants'

TYLENOL® Oral Suspension

active ingredient**

Infants'

Pain Relief

PAIN RELIEVER - FEVER REDUCER

ACETAMINOPHEN

ORAL SUSPENSION

160 mg per 5 mL

- Alcohol Free
- Aspirin Free
- Ibuprofen Free

Use ONLY
enclosed syringe

Grape

Flavor

2 FL OZ (59 mL)

INDEPENDENTLY TESTED
PV
SATISFACTION GUARANTEED

LOT:

EXP:

DO NOT USE IF PRINTED NECK BAND IS BROKEN OR MISSING

BX-077

DISTRIBUTED BY:
PHARMACY VALUE ALLIANCE, LLC
407 EAST LANCASTER AVENUE,
WAYNE, PA 19087

**This product is not manufactured or distributed by
McNeil Consumer Healthcare, distributor of Infants'
Tylenol® Oral Suspension.

IMPORTANT INSTRUCTIONS

1 Remove the cap.

2 Insert the syringe
tip through the
opening at the
top of the bottle.

3 Turn the bottle
upside down and
fill syringe to
dose.

Use enclosed
syringe only.

Do not use other
dosing devices.

INDEPENDENTLY TESTED
PV
SATISFACTION GUARANTEED

If for any reason you are not satisfied
with this product, please return it to the
store where purchased for a full refund.

Product Label - Outer

Product Label - Inner

Premier Value® Infants' Pain Relief

end res